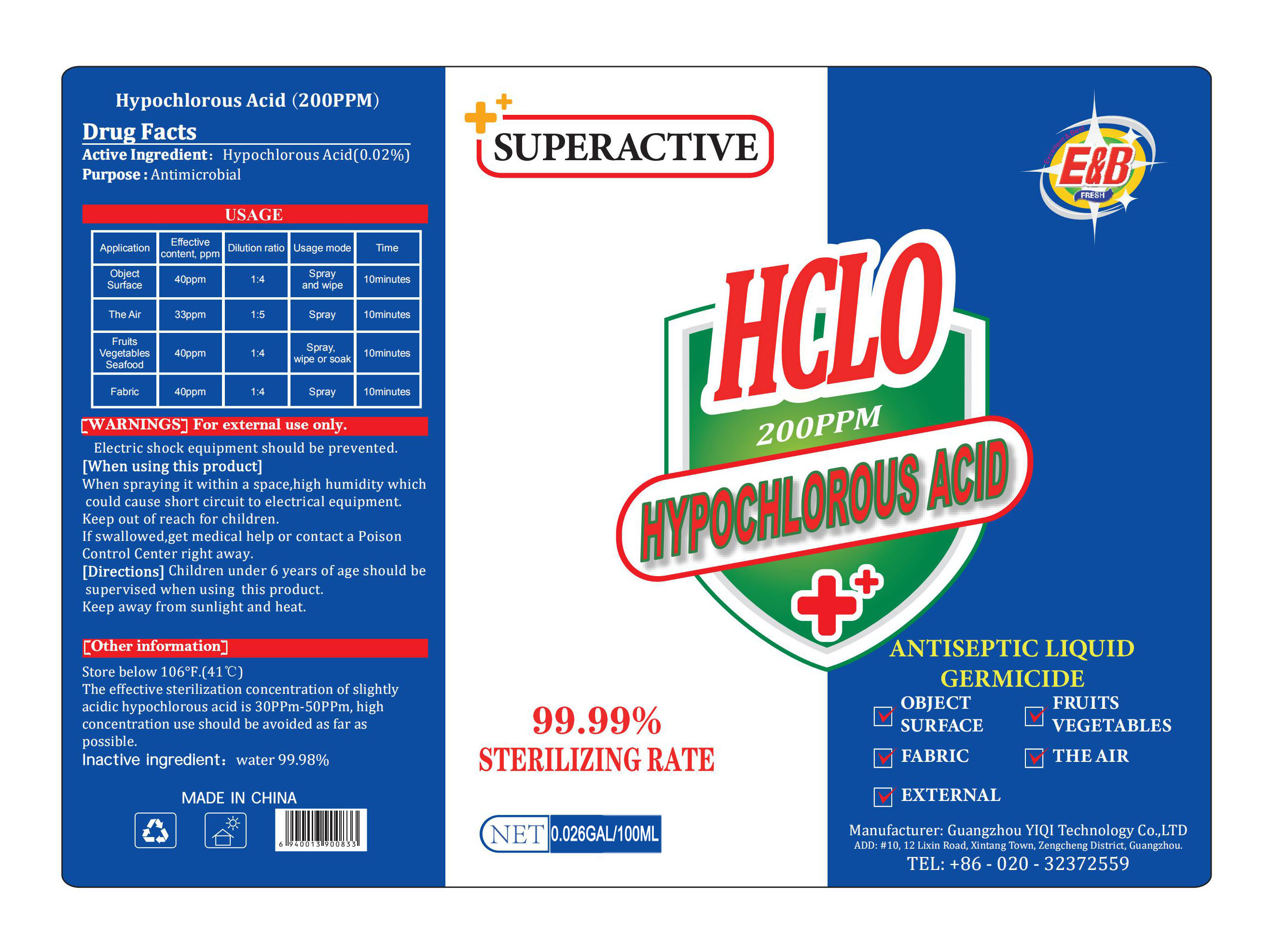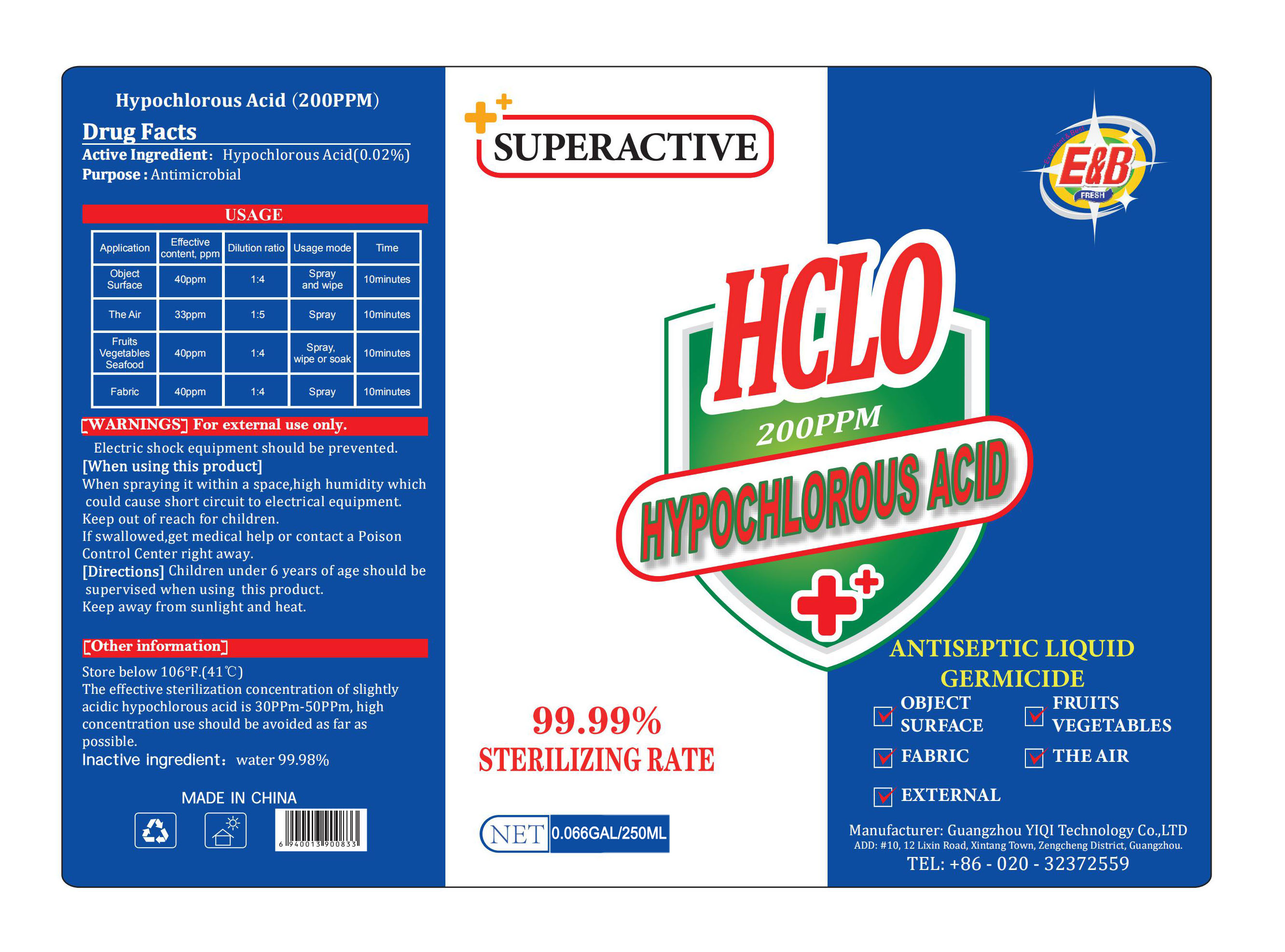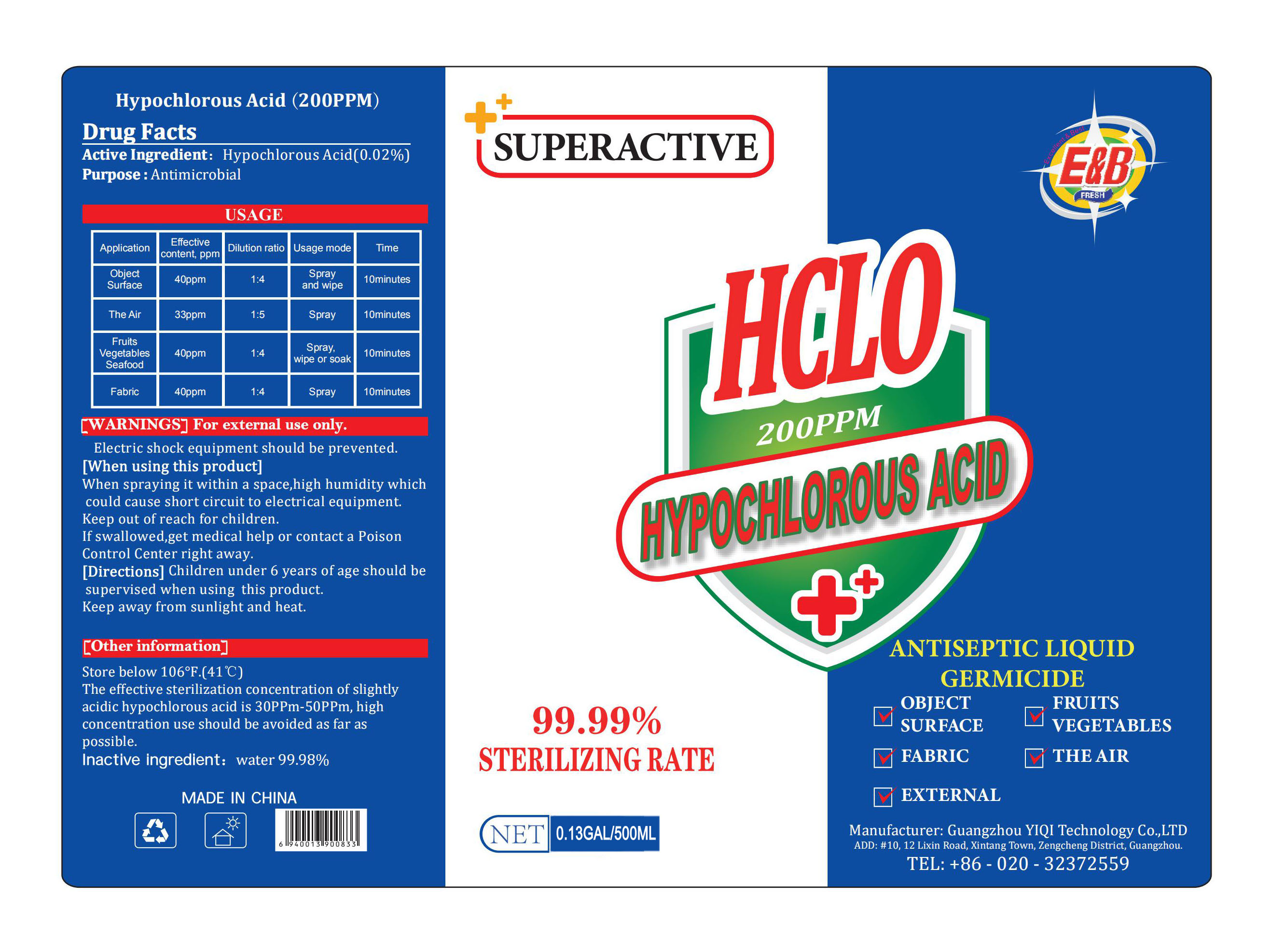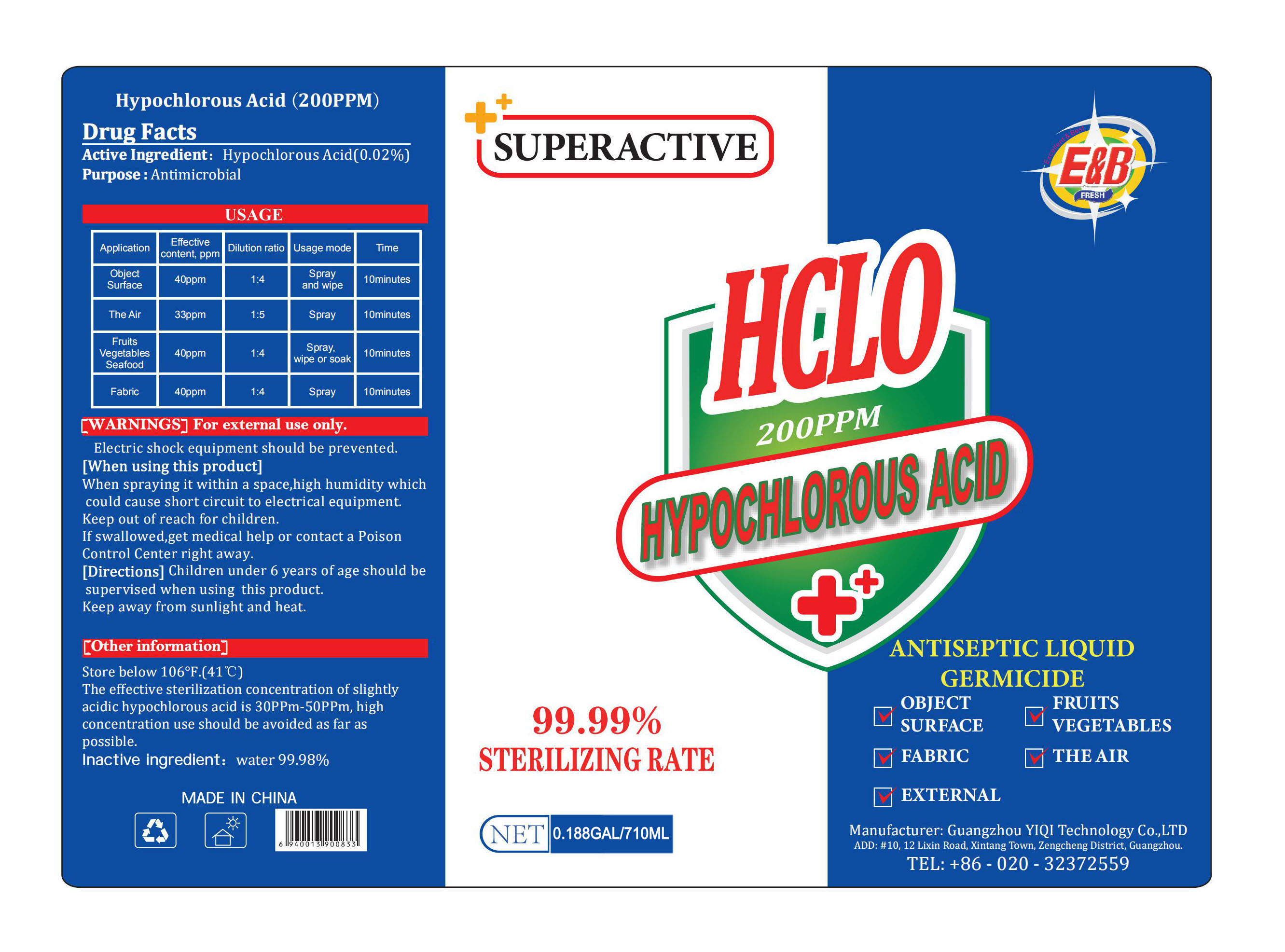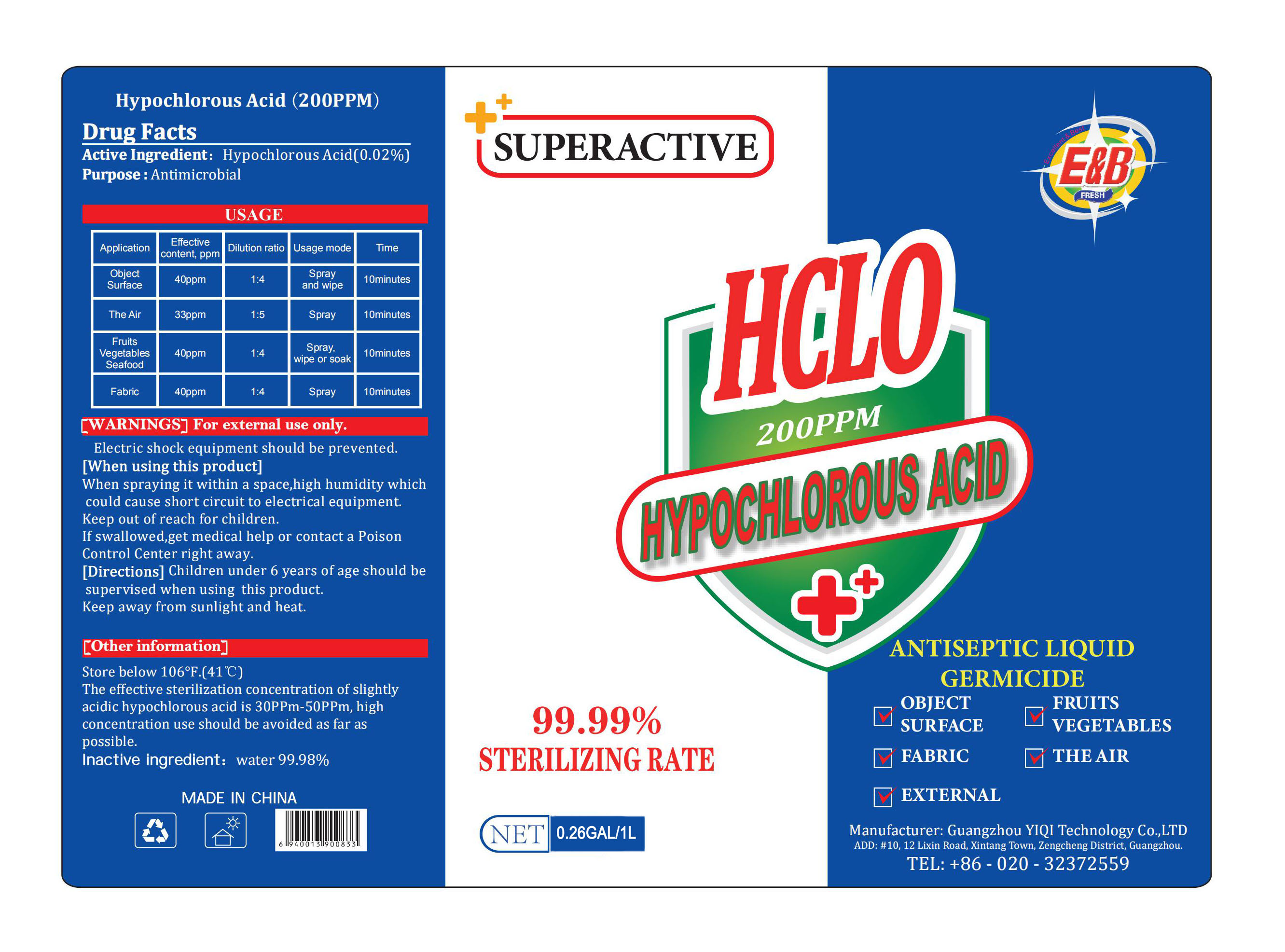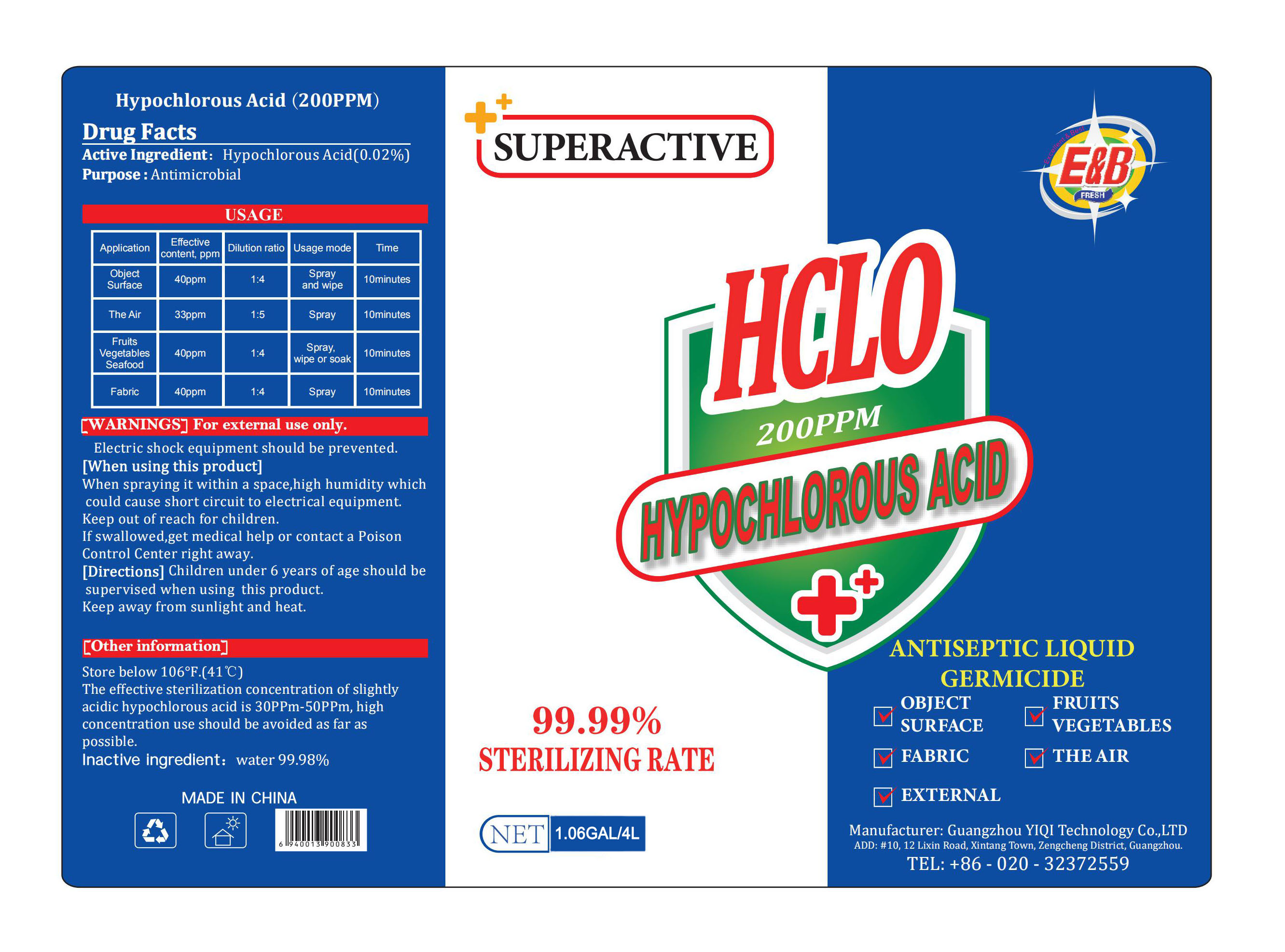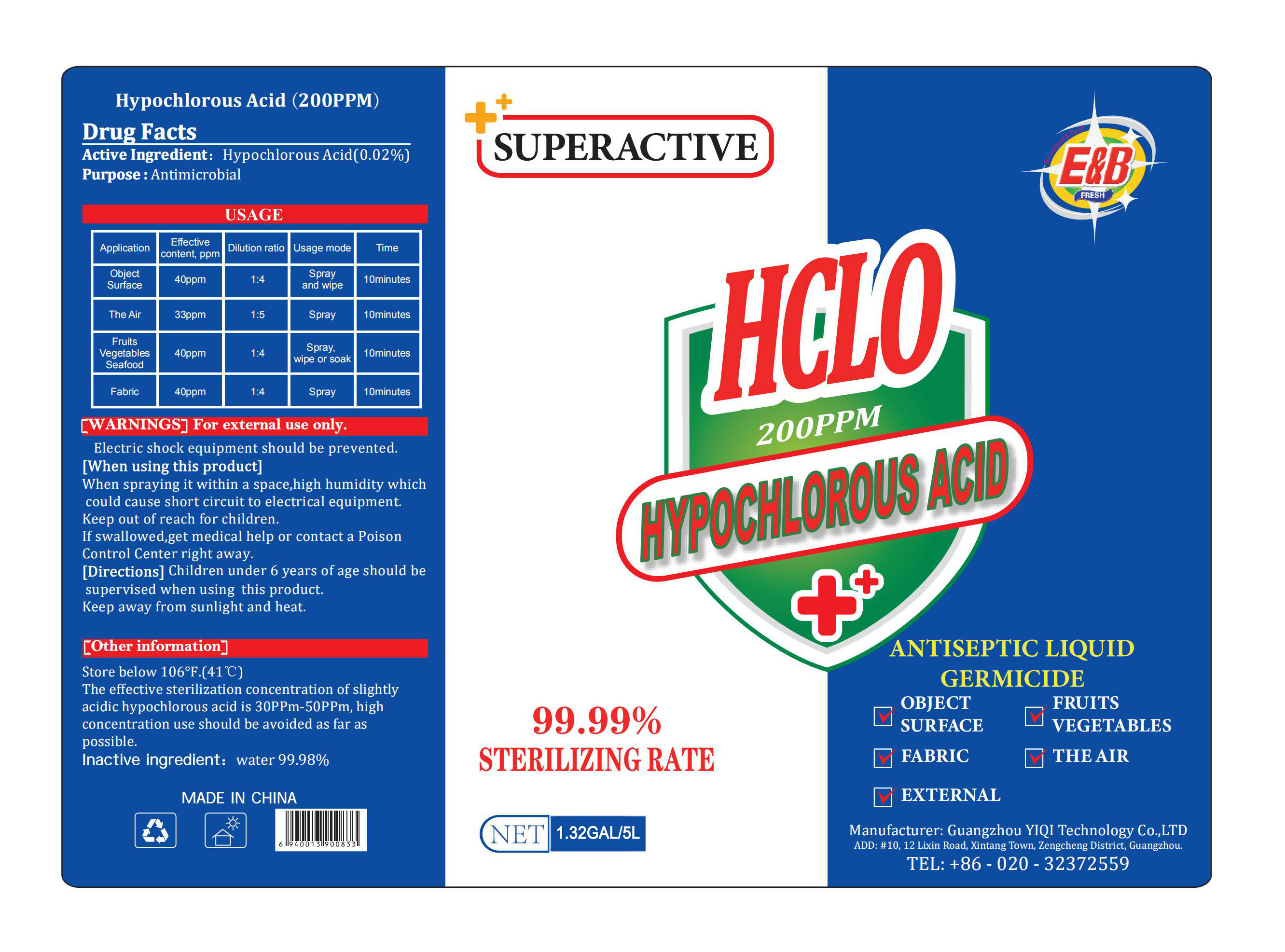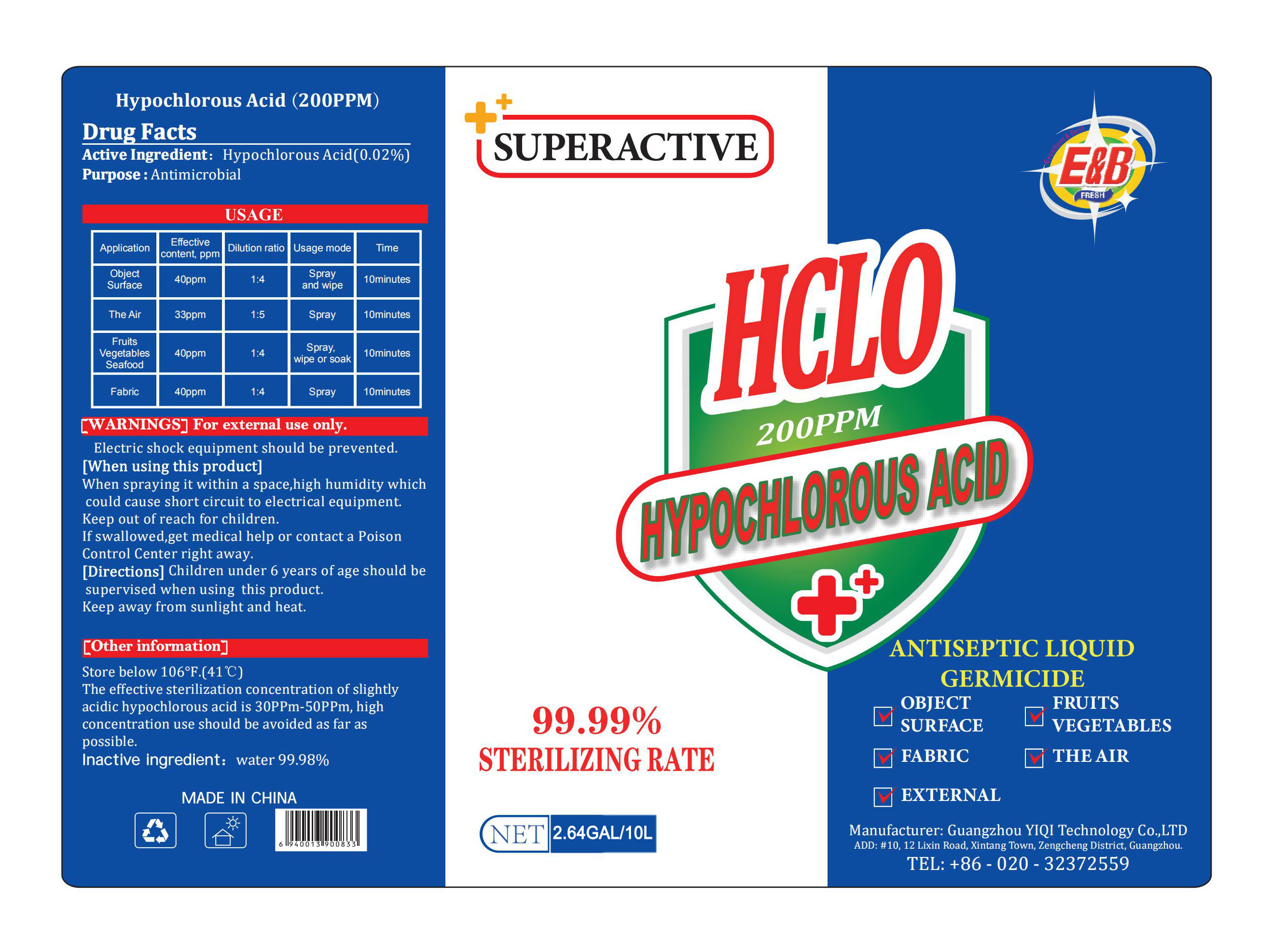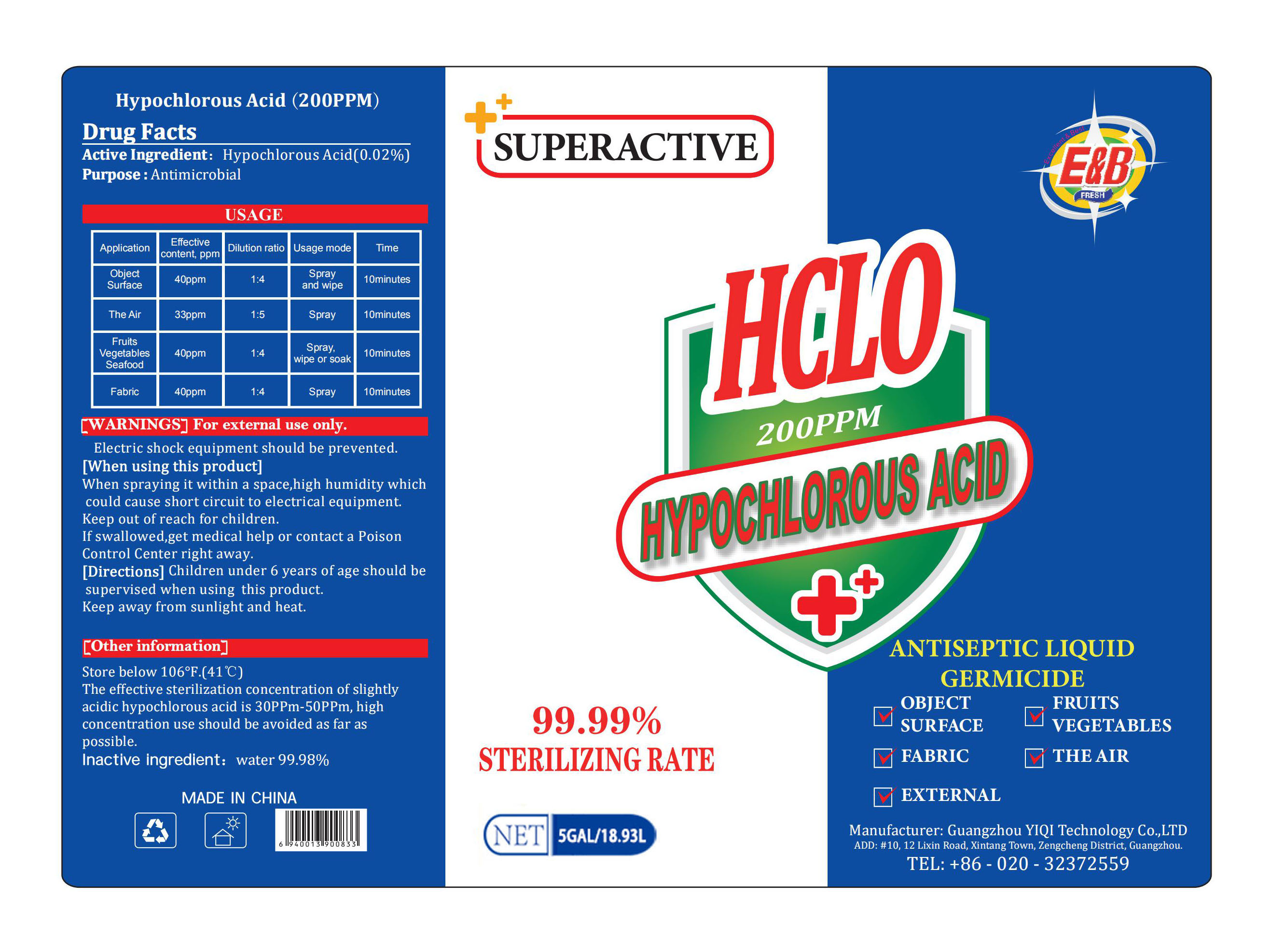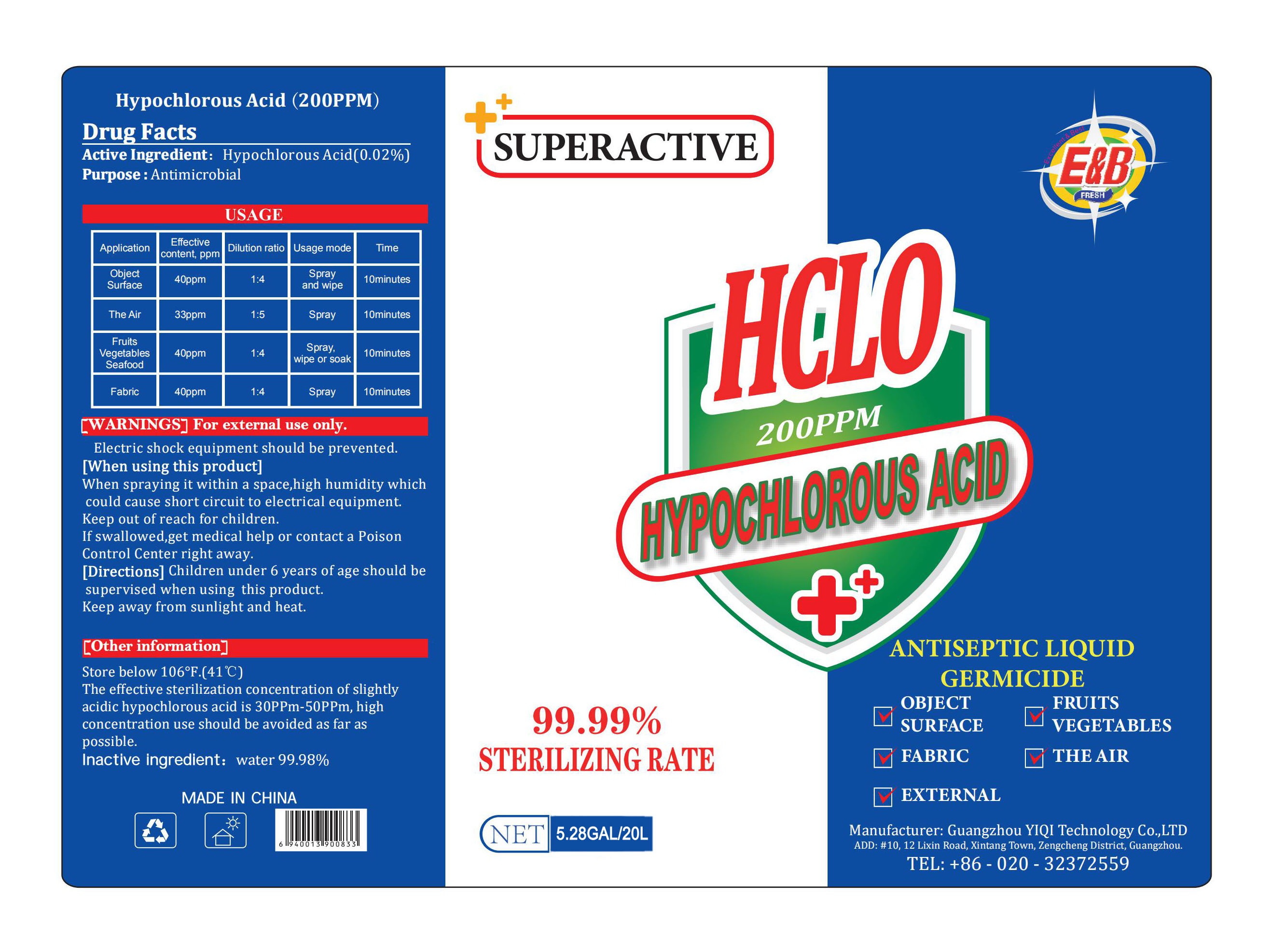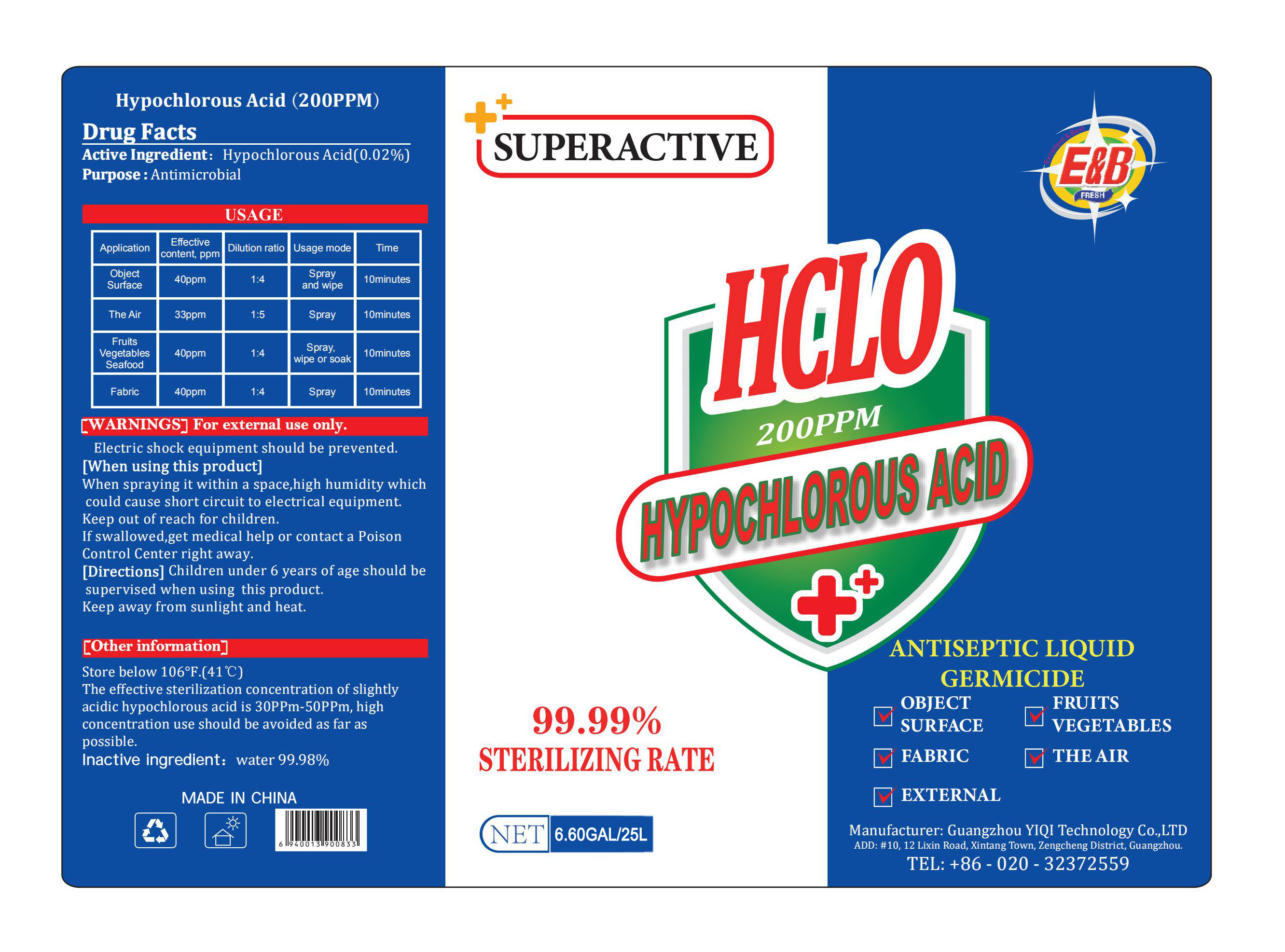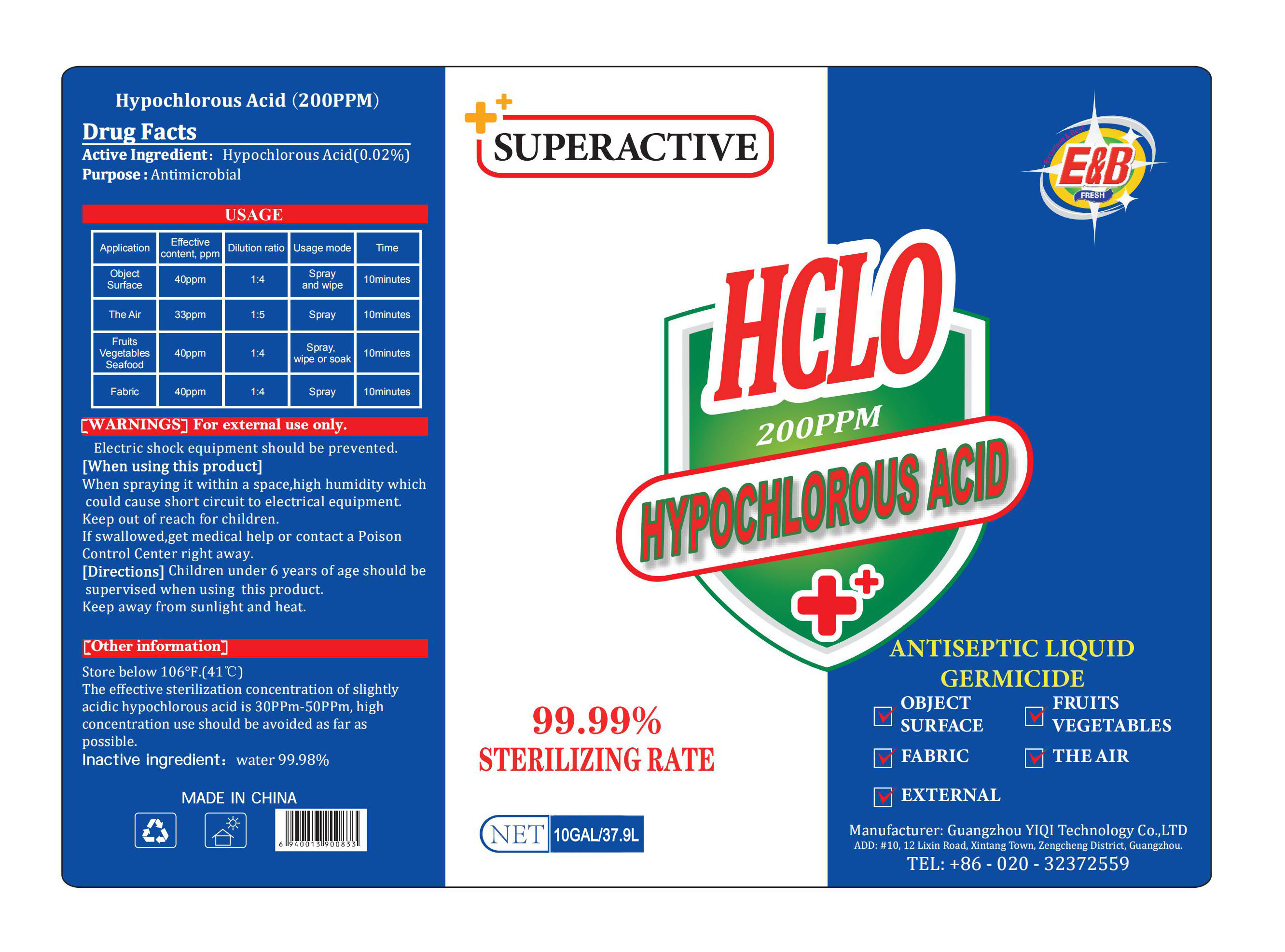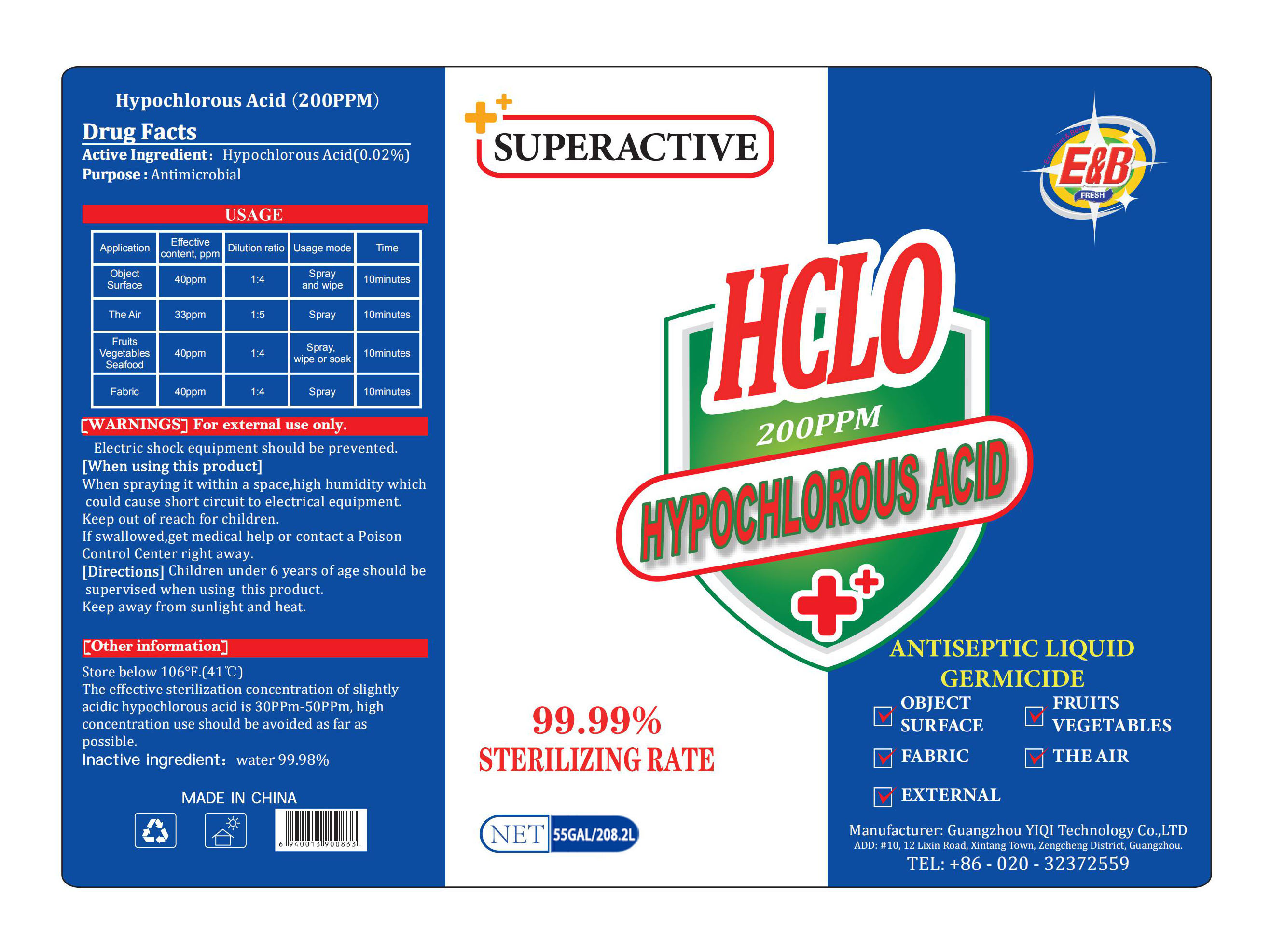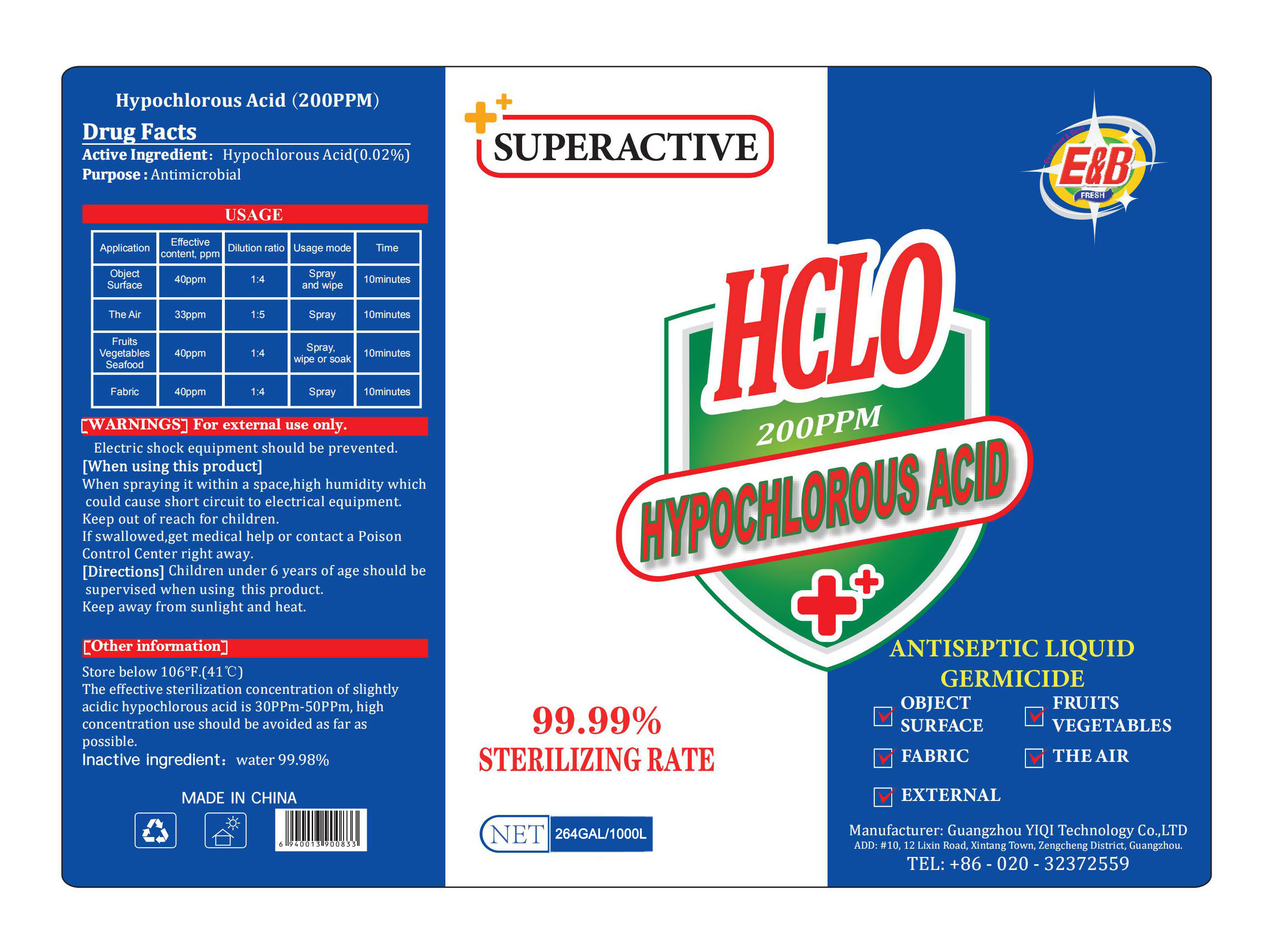 DRUG LABEL: Hypochlorous Acid
NDC: 78295-007 | Form: LIQUID
Manufacturer: GUANGZHOU YIQI TECHNOLOGY CO.,LTD
Category: otc | Type: HUMAN OTC DRUG LABEL
Date: 20201215

ACTIVE INGREDIENTS: HYPOCHLOROUS ACID 0.02 kg/100 L
INACTIVE INGREDIENTS: WATER

78295-007
Hypochlorous Acid

Active ingredient

ActiveIngredient：Hypochlorous Acid(0.02%)

Purpose

Purpose：Antimicrobial

Usage

Application | Effective content, ppm | Dilution ratio | Usage mode | TIME
Object Surface | 40ppm | 1:4 | Spray and wipe | 10minutes
The Air | 33ppm | 1:5 | Spray | 10minutes
Fruits Vegetables Seafood | 40ppm | 1:4 | Spray, wipe or soak | 10minutes
Fabric | 40ppm | 1:4 | Spray | 10minutes

WARNINGS

For external use only.
Electricshock equipment should be prevented.

DO NOT USE

/

When using this product

When spraying it within a space， high humidity which could cause short circuit to electrical equipment.

STOP USE

/

Keep out of reach for children.
If swallowed， get medical help or contact a Poison Control Center right away.

Directions

Children under 6 years of age should be supervised when using this product.
Keep away from sunlight and heat.

Other information

Store below 106F.(41℃)
The effective sterilization concentration of slightly acidic hypochlorous acidis30PPm-50PPm， high concentration use should be avoided as far as possible.

Inactive ingredient

water 99.98%